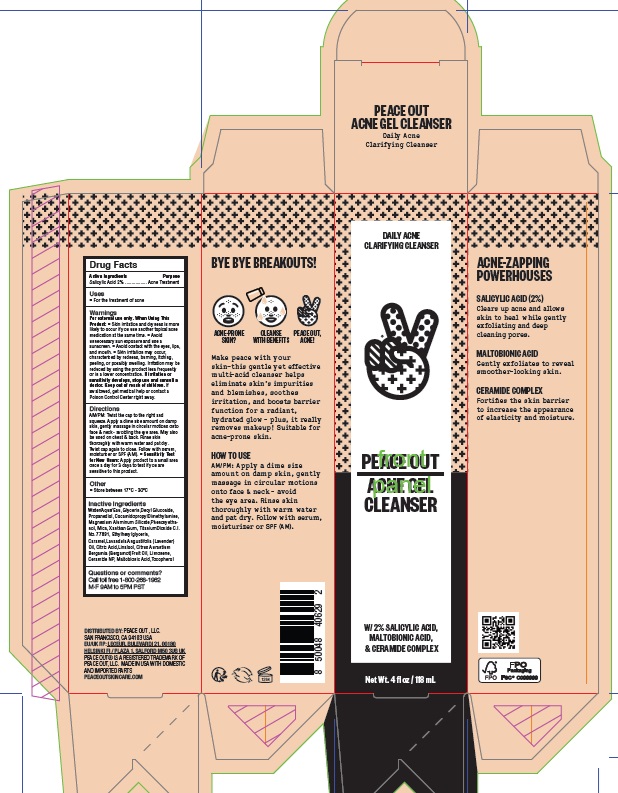 DRUG LABEL: Peace Out Acne Cleanser
NDC: 71494-103 | Form: GEL
Manufacturer: Peace Out LLC
Category: otc | Type: HUMAN OTC DRUG LABEL
Date: 20260129

ACTIVE INGREDIENTS: SALICYLIC ACID 20 mg/1 mL
INACTIVE INGREDIENTS: CARAMEL; LAVENDER OIL; CITRIC ACID MONOHYDRATE; LINALOOL, (+)-; BERGAMOT OIL; LIMONENE, (+)-; CERAMIDE NP; WATER; DECYL GLUCOSIDE; MAGNESIUM ALUMINUM SILICATE; PHENOXYETHANOL; MICA; TITANIUM DIOXIDE; ETHYLHEXYLGLYCERIN; MALTOBIONIC ACID; GLYCERIN; PROPANEDIOL; COCAMIDOPROPYL DIMETHYLAMINE; TOCOPHEROL; XANTHAN GUM

Peace Out Acne Gel Cleanser

Active Ingredients

Salicylic Acid 2%

Purpose

Acne Treatment

Uses

- For the treatment of acne

Warnings

For external use only.

When Using This Product:

- Skin irritation and dryness is more likely to occur if you use another topical acne medication at the same time.
- Avoid unnecessary sun exposure and use a sunscreen.
- Avoid contact with the eyes, lips, and mouth.
- Skin irritation may occur, characterized by redness, burning, itching, peeling, or possibly swelling. Irritation may be reduced by using the product less frequently or in a lower concentration. If irritation or sensitivity develops, stop use and consult a doctor.

Keep out of reach of children.

If swallowed, get medical help or contact a Poison Control Center right away.

Directions

AM/PM: Twist the cap to the right and squeeze. Apply a dime size amount on damp skin, gently massage in circular motions onto face & neck - avoiding the eye area. May also be used on chest & back. Rinse skin thoroughly with warm water and pat dry. Twist cap again to close. Follow with serum, moisturizer or SPF (AM).

- Sensitivity Test for New Users: Apply product to a small area once a day for 3 days to test if you are sensitive to this product.

Other

- Store between 17°C - 30°C

Inactive Ingredients

Water/Aqua/Eau, Glycerin,Decyl Glucoside, Propanediol, CocamidopropylDimethylamine, Magnesium Aluminum Silicate,Phenoxyethanol, Mica, Xanthan Gum, TitaniumDioxide C.I. No. 77891, Ethylhexylglycerin, Caramel,Lavandula Angustifolia (Lavender) Oil, Citric Acid,Linalool, Citrus Aurantium Bergamia (Bergamot)Fruit Oil, Limonene, Ceramide NP, Maltobionic Acid,Tocopherol

Questions or comments?

Call toll free 1-800-268-1962
M-F 9AM to 5PM PST